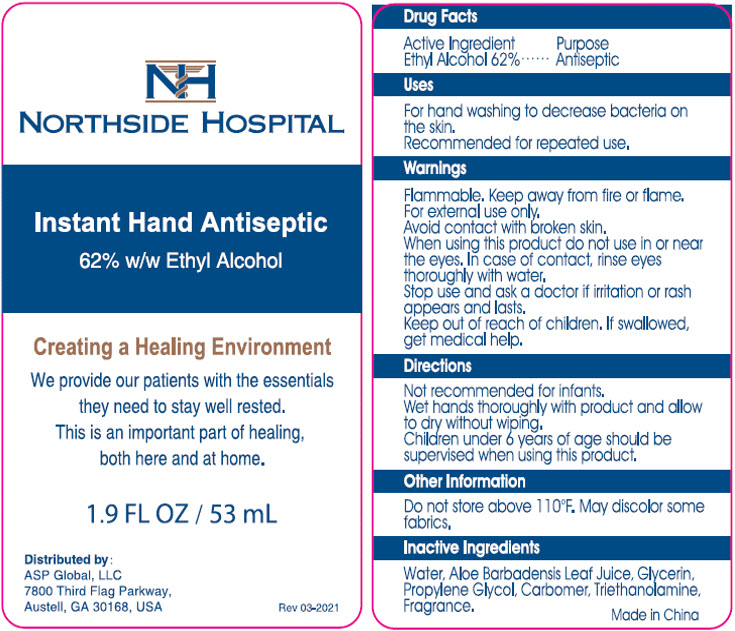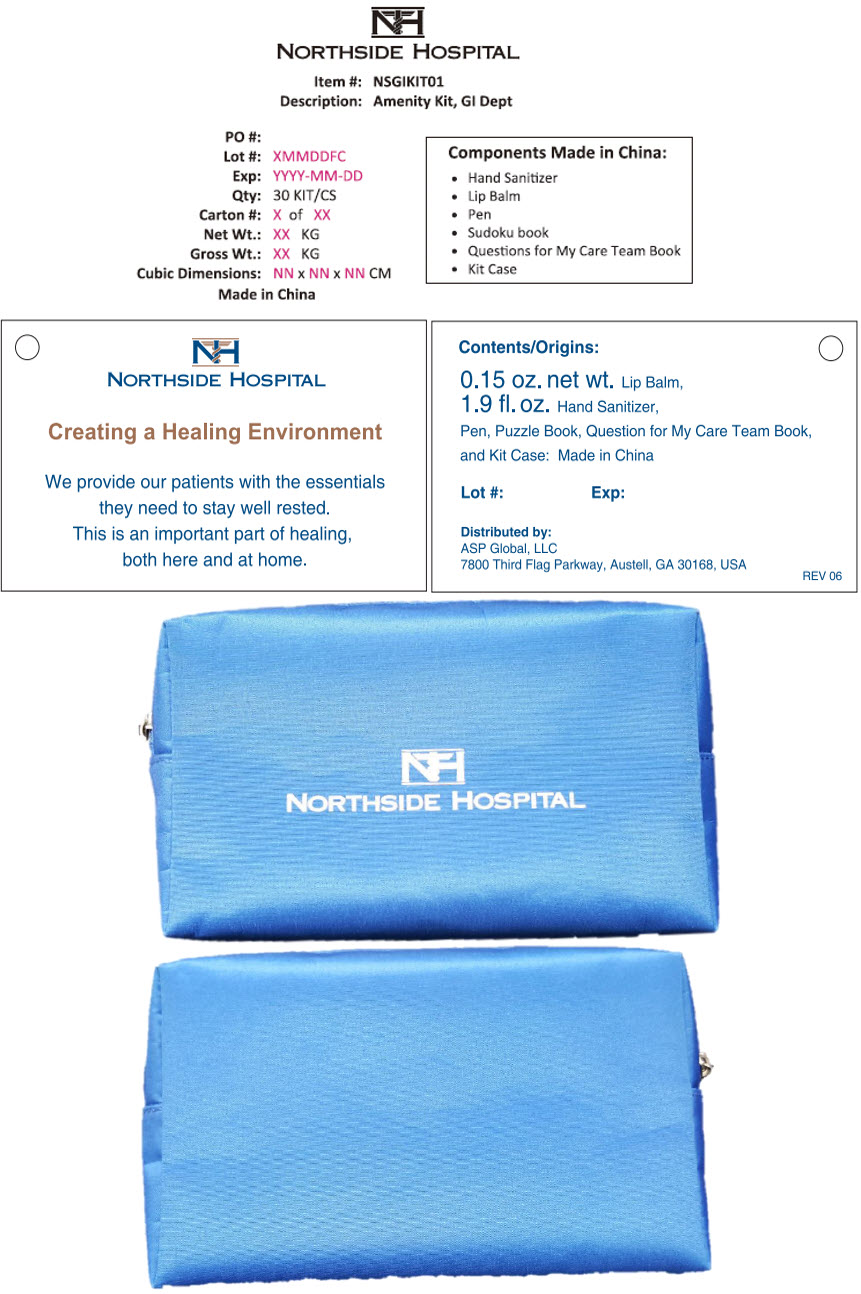 DRUG LABEL: Northside Hospital Amenity Kit--GI Dept
NDC: 59448-201 | Form: KIT | Route: TOPICAL
Manufacturer: ASP Global, LLc
Category: otc | Type: HUMAN OTC DRUG LABEL
Date: 20240110

ACTIVE INGREDIENTS: Alcohol 62 mL/100 mL
INACTIVE INGREDIENTS: Water; Aloe Vera Leaf; Glycerin; Propylene Glycol; Carbomer Interpolymer Type A (Allyl Sucrose Crosslinked); Trolamine

Northside Hospital Amenity Kit--GI Dept

Drug Facts

Active Ingredient

Ethyl Alcohol 62%

Purpose

Antiseptic

Uses

For hand washing to decrease bacteria on the skin.

Recommended for repeated use.

Warnings

Flammable. Keep away from fire or flame.

For external use only.

Avoid contact with broken skin.

When using this product do not use in or near the eyes. In case of contact, rinse eyes thoroughly with water.

Stop use and ask a doctor if irritation or rash appears and lasts.

Keep out of reach of children.If swallowed, get medical help.

Directions

Not recommended for infants.

Wet hands thoroughly with product and allow to dry without wiping.

Children under 6 years of age should be supervised when using this product.

Other Information

Do not store above 110°F. May discolor some fabrics.

Inactive Ingredients

Water, Aloe Barbadensis Leaf Juice, Glycerin, Propylene Glycol, Carbomer, Triethanolamine, Fragrance.

Distributed by:
ASP Global, LLC
7800 Third Flag Parkway,
Austell, GA 30168, USA

PRINCIPAL DISPLAY PANEL - 53 mL Bottle Label

NORTHSIDE HOSPITAL

Instant Hand Antiseptic
62% w/w Ethyl Alcohol

Creating a Healing Environment

We provide our patients with the essentials
they need to stay well rested.
This is an important part of healing,
both here and at home.

1.9 FL OZ / 53 mL

Distributed by:
ASP Global, LLC
7800 Third Flag Parkway,
Austell, GA 30168, USA

Rev 03-2021

PRINCIPAL DISPLAY PANEL - Kit Label

NORTHSIDE HOSPITAL

Item #: NSGIKIT01
Description: Amenity Kit, GI Dept

PO #:
Lot #: XMMDDFC
Exp: YYYY-MM-DD
Qty: 30 KIT/CS
Carton #: X of XX
Net Wt.: XX KG
Gross Wt.: XX KG
Cubic Dimensions: NN x NN x NN CM
Made in China

Components Made in China:

- Hand Sanitizer
- Lip Balm
- Pen
- Sudoku book
- Questions for My Care Team Book
- Kit Case

NORTHSIDE HOSPITAL

Creating a Healing Environment

We provide our patients with the essentials
they need to stay well rested.
This is an important part of healing,
both here and at home.

Contents/Origins:

0.15 oz. net wt. Lip Balm,
1.9 fl. oz. Hand Sanitizer,
Pen, Puzzle Book, Question for My Care Team Book,
and Kit Case: Made in China

Lot #:
Exp:

Distributed by:
ASP Global, LLC
7800 Third Flag Parkway, Austell, GA 30168, USA

REV 06

NORTHSIDE HOSPITAL